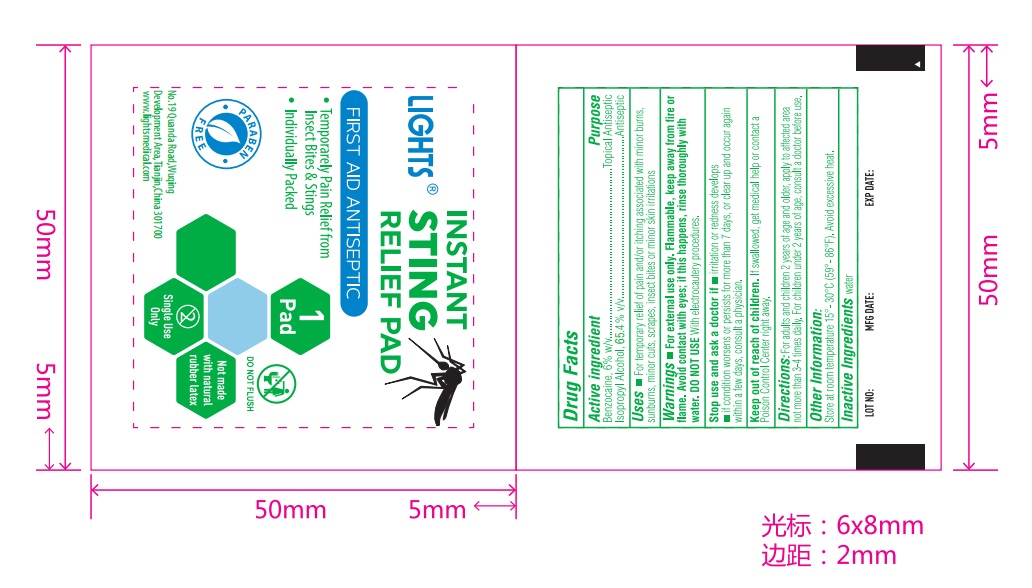 DRUG LABEL: LIGHTS Instant Sting Relief Pad
NDC: 61333-215 | Form: SOLUTION
Manufacturer: Lights Medical Manufacture Co., Ltd.
Category: otc | Type: HUMAN OTC DRUG LABEL
Date: 20260121

ACTIVE INGREDIENTS: BENZOCAINE 6 g/100 mL; ISOPROPYL ALCOHOL 65.4 mL/100 mL
INACTIVE INGREDIENTS: WATER

61333-215 Light Instant Sting Relief Pad

Active Ingredient

Benzocaine 6% w/v

Isopropyl Alcohol: 65.4% v/v

Purpose

Topical Anesthetic

Antiseptic

INDICATIONS AND USAGE

Uses: For temporary relief of pain and itching associated with minor burns, sunburns, minor cut, scrapes, insect bites, or minor skin irritations

Warnings:

For external use only. Flammable, keep away from fire or flame. Avoid contact with eyes, if this happens, rinse throughly with water. DO NOT USE with electrocautery procedures.

Stop use and ask a doctor if

- irritation or redness develops
- if condition worsens or persists for more than 7 days, or clear up and occur again within a few days, consult a physician

Keep out of reach of children. If swallowed, get medical help or contact a Poison Control Center right away

Directions

For adults and children 2 yeas of age or older: Apply to affected area not more than 3-4 times daily

Children under 2 yeas of age: Consult a doctor before use

Other Information

Store at room temperature 15-30 C (59-86F). Avoid excessive heat.

Inactive Ingredient

Purified Water